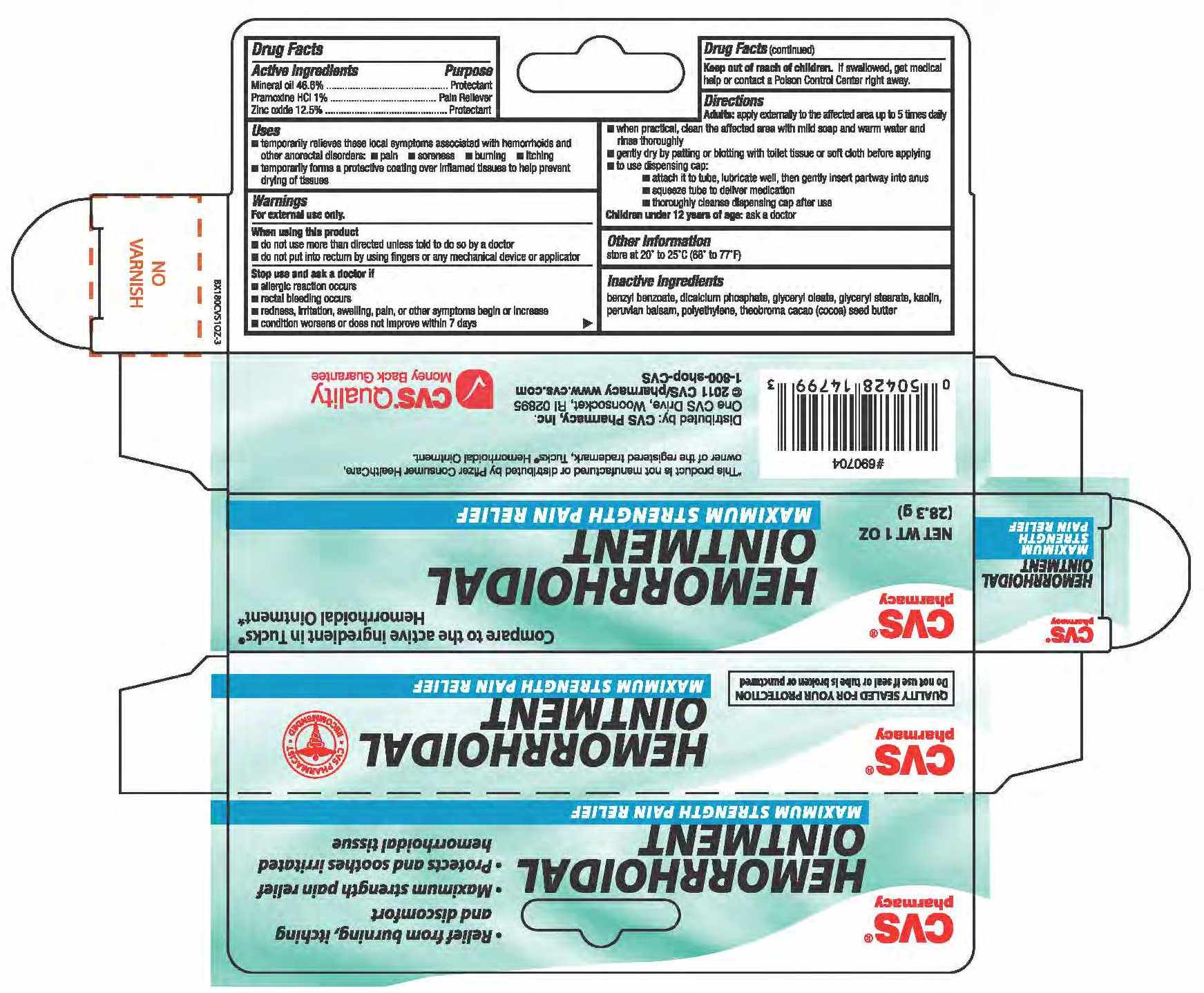 DRUG LABEL: MINERAL OIL, PRAMOXINE HYDROCHLORIDE AND ZINC OXIDE
NDC: 59779-399 | Form: CREAM
Manufacturer: CVS Pharmacy
Category: otc | Type: HUMAN OTC DRUG LABEL
Date: 20100716

ACTIVE INGREDIENTS: MINERAL OIL 466 mg/1 g; PRAMOXINE HYDROCHLORIDE 10 mg/1 g; ZINC OXIDE 125 mg/1 g
INACTIVE INGREDIENTS: COCOA BUTTER; GLYCERYL MONOSTEARATE; GLYCERYL MONOOLEATE; KAOLIN; BALSAM PERU; BENZYL BENZOATE; CALCIUM PHOSPHATE

drug facts

Active ingredients Purpose
Mineral Oil 46.8%.............................................Protectant
Pramoxine HCL 1%......................................... Pain Reliever
Zinc Oxide 12.5%............................................Protectant

Active ingredients Purpose
Mineral Oil 46.8%.............................................Protectant
Pramoxine HCL 1%......................................... Pain Reliever
Zinc Oxide 12.5%............................................Protectant
Uses
- temporarily relieves these local symptoms associated with hemorrhoids and other anorectal disorders:
- pain - soreness - burning - itching
- temporarily forms a protective coating over inflamed tissues to help prevent drying of tissues

Keep out of reach of children. If swallowed, get medical help or contact
a Poison Control Center right away.

Uses
- temporarily relieves these local symptoms associated with hemorrhoids and other anorectal disorders:
- pain - soreness - burning - itching
- temporarily forms a protective coating over inflamed tissues to help prevent drying of tissues
Other information - store at 20 degrees - 25 degrees C (68 degrees - 77 degrees F)

Warnings
For external use only.
When using this product
- do not use more than directed unless told to do so by a doctor
- do not put into rectum by using fingers or any mechanical device or applicator
Stop use and ask a doctor if
- allergic reaction occurs
- rectal bleeding occurs
- redness, irritation, swelling pain or other symptoms begin or increase
- condition worsens, or does not improve within 7 days
Keep out of the reach of children. If swallowed, get medical help or contact a Poison Control Center right away

Directions
Adults: apply externally to the affected area up to 5 times daily
- when practical, clean the affected area with mild soap and warn water and rinse thoroughly
- gently dry by patting or blotting with toilet tissue or soft cloth before applying
- to use dispensing cap:
- attach it to tube, lubricate well, then gently insert partway into anus
- squeeze tube to deliver medication
- thoroughly cleanse dispensing cap after use
Children under 12 years of age: ask a doctor

Inactive Ingredients
benzyl benzonate, dicalcium phosphate, glyceryl oleate, glyceryl stearate,
kaolin, peruvian balsam, polyethylene, theobroma cacao (cocoa) seed butter